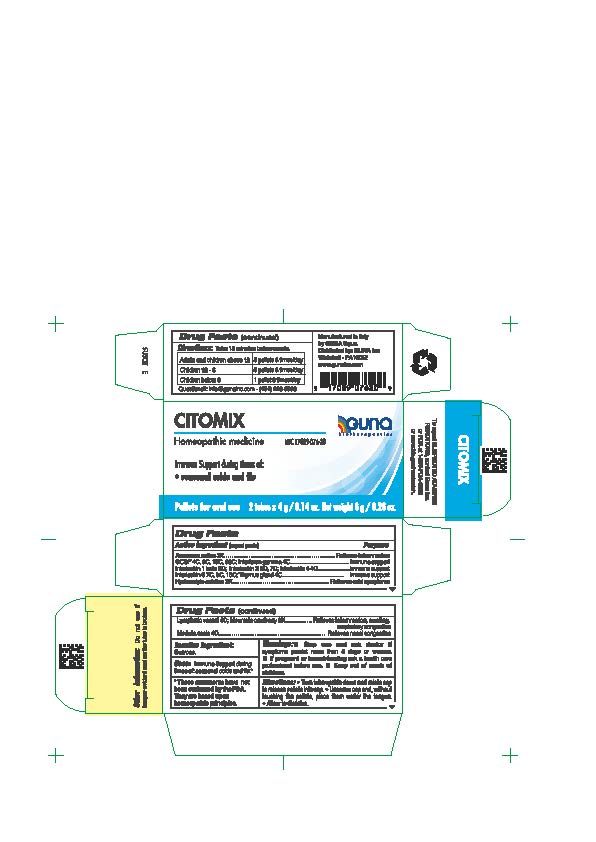 DRUG LABEL: CITOMIX
NDC: 17089-076 | Form: PELLET
Manufacturer: Guna spa
Category: homeopathic | Type: HUMAN OTC DRUG LABEL
Date: 20250110

ACTIVE INGREDIENTS: PINEAPPLE 3 [hp_X]/4 g; LENOGRASTIM 4 [hp_C]/4 g; CENTELLA ASIATICA 3 [hp_X]/4 g; INTERFERON GAMMA-1B 4 [hp_C]/4 g; CANAKINUMAB 5 [hp_C]/4 g; ALDESLEUKIN 5 [hp_C]/4 g; BINETRAKIN 4 [hp_C]/4 g; HUMAN INTERLEUKIN-6 (NONGLYCOSYLATED) 7 [hp_C]/4 g; SUS SCROFA SMALL INTESTINE MUCOSA LYMPH FOLLICLE 4 [hp_C]/4 g; SUS SCROFA BONE MARROW 4 [hp_C]/4 g; CRANBERRY 3 [hp_X]/4 g; SUS SCROFA THYMUS 4 [hp_C]/4 g
INACTIVE INGREDIENTS: SUCROSE 3.5 g/4 g

CITOMIX

ACTIVE INGREDIENTS/PURPOSE

ANANASSA SATIVA 3X RELIEVES INFLAMMATION
GCSF 4C, 9C, 15C, 30C, INTERFERON GAMMA 4C IMMUNE SUPPORT
INTERLEUKIN 1 BETA 5C, INTERLEUKIN 2 5C, 7C, INTERLEUKIN 4 4C IMMUNE SUPPORT
INTERLEUKIN 6 7C, 9C, 15C, THYMUS GLAND 4C IMMUNE SUPPORT

HYDROCOTYLE ASIATICA 3X RELIEVES COLD SYMPTOMS

LYMPHATIC VESSEL 4C, MOUNTAIN CRANBERRY 3X RELIEVES INFLAMMATION, SWELLING, RESPIRATORY CONGESTION

MEDULLA OSSIS 4C RELIEVES NASAL CONGESTION

USES

Immune Support during times of:

- seasonal colds and flu

WARNINGS

- Stop use and ask doctor if symptoms persist more than 5 days or worsen.

PREGNANCY

If pregnant or breast-feeding ask a health care professional before use.

WARNINGS

Keep this and all medicines out of reach of children

DIRECTIONS

- Turn tube upside down and rotate cap to release pellets into cap.
- Unscrew cap and without touching pellets tip them into the mouth under the tongue.
- Allow to dissolve
- Take 15 minutes before meals.

QUESTIONS

Questions?: info@gunainc.com
tel. (484) 223-3500

DOSAGE AND ADMINISTRATION

- Take 15 minutes before meals
- Adults and children 12 years and older 5 pellets 3 times per day
- Children between 12 years and 6 years of age 3 pellets 3 times per day
- Children under 6 years 1 pellet 3 times per day to be disoolved into a little water

- Stop use and ask doctor if symptoms persist more than 5 days or worsen.
- If pregnant or breast-feeding ask a health professional before use.
- Keep out of reach of children.

Inactive ingredient: Sucrose.

INDICATIONS AND USAGE

Immune support suring times of:

- Seasonal colds and flu

- Keep out of reach of children